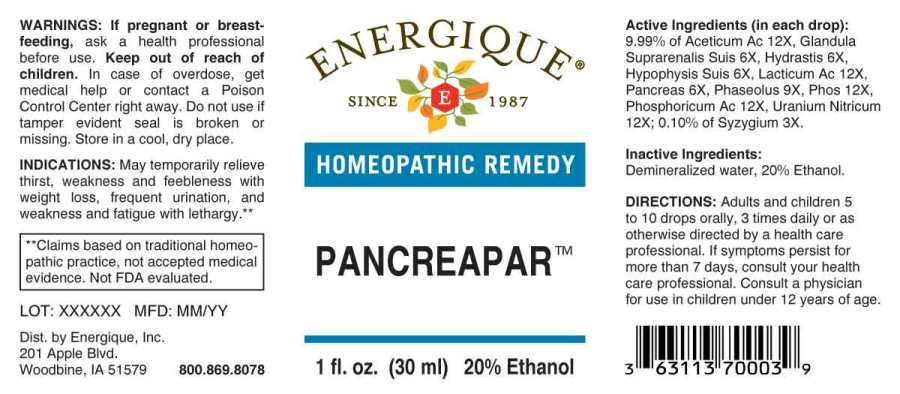 DRUG LABEL: Pancreapar
NDC: 44911-0420 | Form: LIQUID
Manufacturer: Energique, Inc.
Category: homeopathic | Type: HUMAN OTC DRUG LABEL
Date: 20230824

ACTIVE INGREDIENTS: SYZYGIUM CUMINI SEED 3 [hp_X]/1 mL; SUS SCROFA ADRENAL GLAND 6 [hp_X]/1 mL; GOLDENSEAL 6 [hp_X]/1 mL; SUS SCROFA PITUITARY GLAND 6 [hp_X]/1 mL; SUS SCROFA PANCREAS 6 [hp_X]/1 mL; KIDNEY BEAN 9 [hp_X]/1 mL; ACETIC ACID 12 [hp_X]/1 mL; LACTIC ACID 12 [hp_X]/1 mL; PHOSPHORIC ACID 12 [hp_X]/1 mL; PHOSPHORUS 12 [hp_X]/1 mL; URANYL NITRATE HEXAHYDRATE 12 [hp_X]/1 mL
INACTIVE INGREDIENTS: WATER; ALCOHOL

Drug Facts:

ACTIVE INGREDIENTS:

(in each drop): 9.99% of Aceticum Acidum 12X, Glandula Suprarenalis Suis 6X, Hydrastis Canadensis 6X, Hypophysis Suis 6X, Lacticum Acidum 12X, Pancreas Suis 6X, Phaseolus 9X, Phosphorus 12X, Phosphoricum Acidum 12X, Uranium Nitricum 12X; 0.10% of Syzygium Jambolanum 3X.

INDICATIONS:

May temporarily relieve thirst, weakness and feebleness with weight loss, frequent urination, and weakness and fatigue with lethargy.

**Claims based on traditional homeopathic practice, not accepted medical evidence. Not FDA evaluated.

WARNINGS:

If pregnant or breast-feeding, ask a health professional before use.

Keep out of reach of children. In case of overdose, get medical help or contact a Poison Control Center right away.

Do not use if tamper evident seal is broken or missing. Store in a cool, dry place.

Keep out of reach of children. In case of overdose, get medical help or contact a Poison Control Center right away.

DIRECTIONS:

Adults and children 5 to 10 drops orally, 3 times daily or as otherwise directed by a health care professional. If symptoms persist for more than 7 days, consult your health care professional. Consult a physician for use in children under 12 years of age.

INDICATIONS:

May temporarily relieve thirst, weakness and feebleness with weight loss, frequent urination, and weakness and fatigue with lethargy.

**Claims based on traditional homeopathic practice, not accepted medical evidence. Not FDA evaluated.

INACTIVE INGREDIENTS:

Demineralized water, 20% Ethanol.

QUESTIONS:

Dist. by Energique, Inc.

201 Apple Blvd

Woodbine, IA 51579 800.869.8078

PACKAGE LABEL DISPLAY:

ENERGIQUE
SINCE 1987
HOMEOPATHIC REMEDY
PANCREAPAR
1 fl. oz. (30 ml)